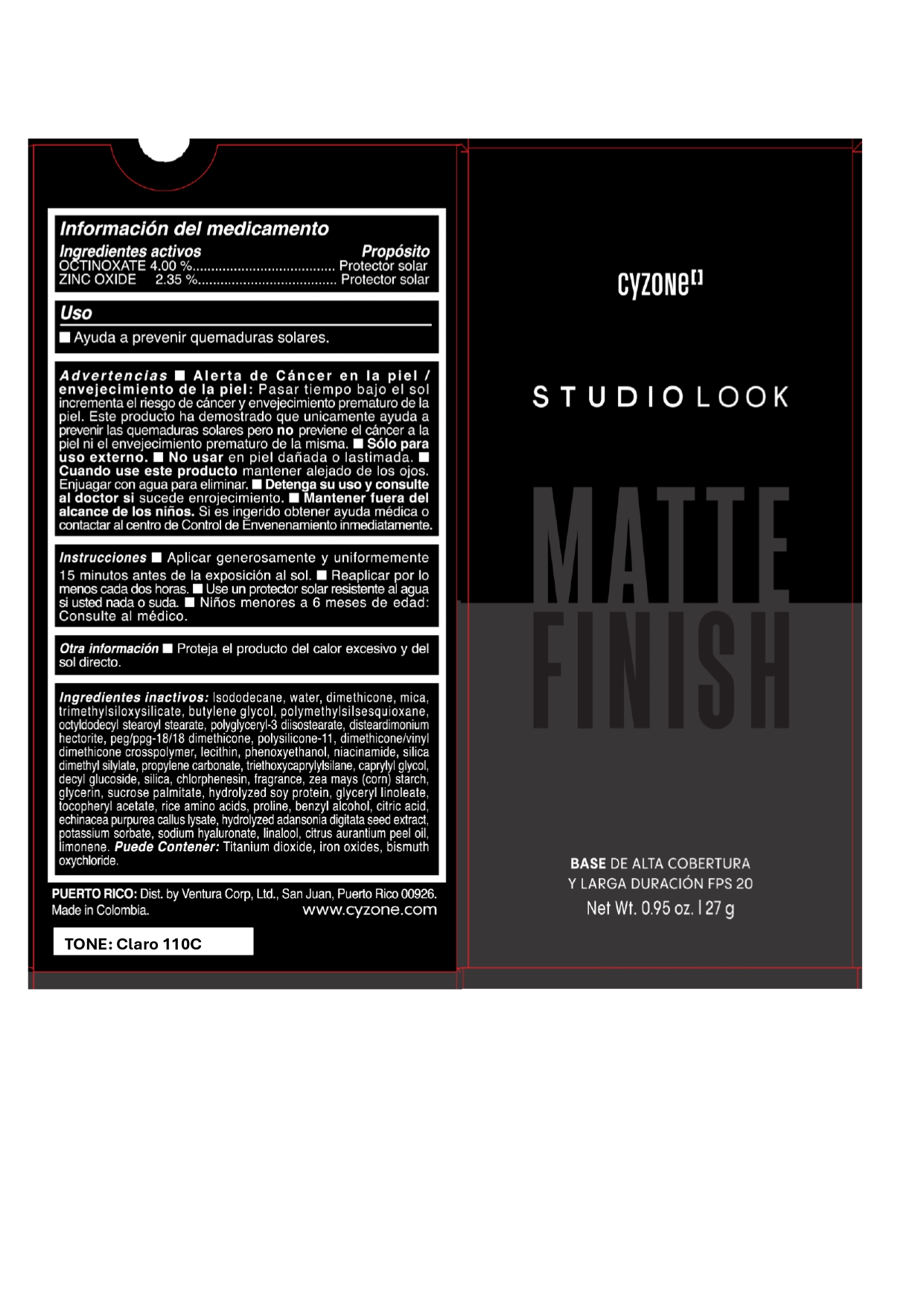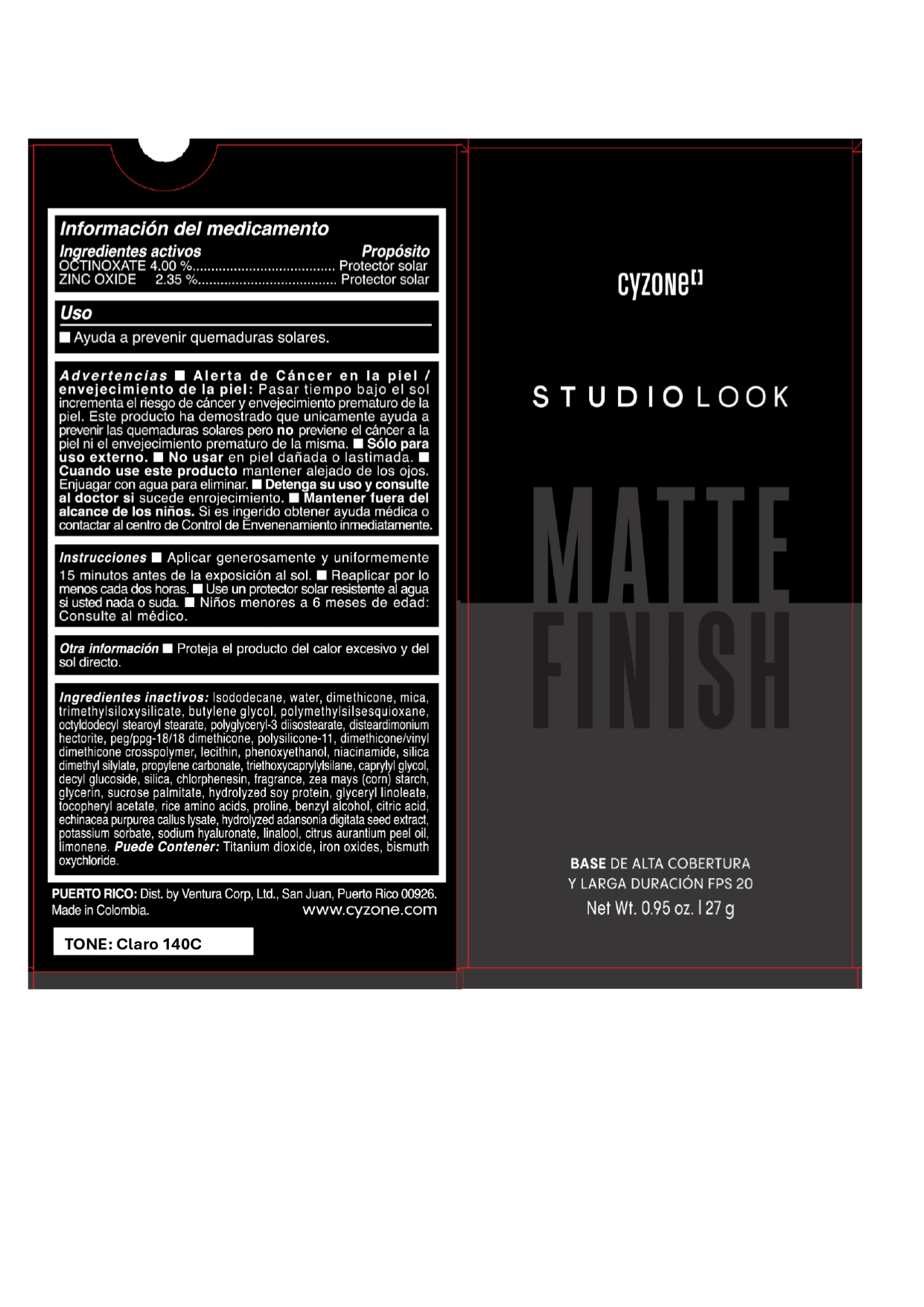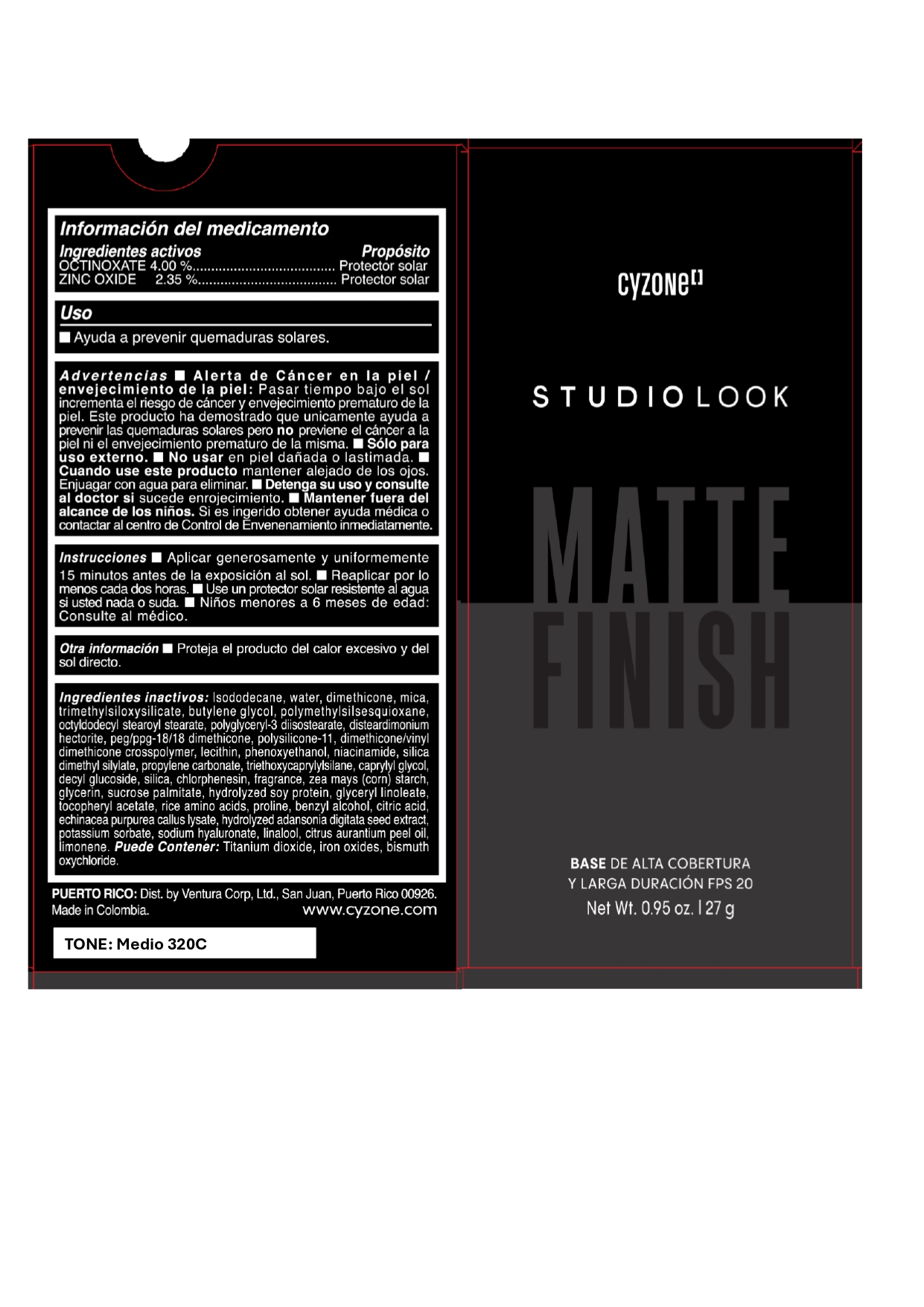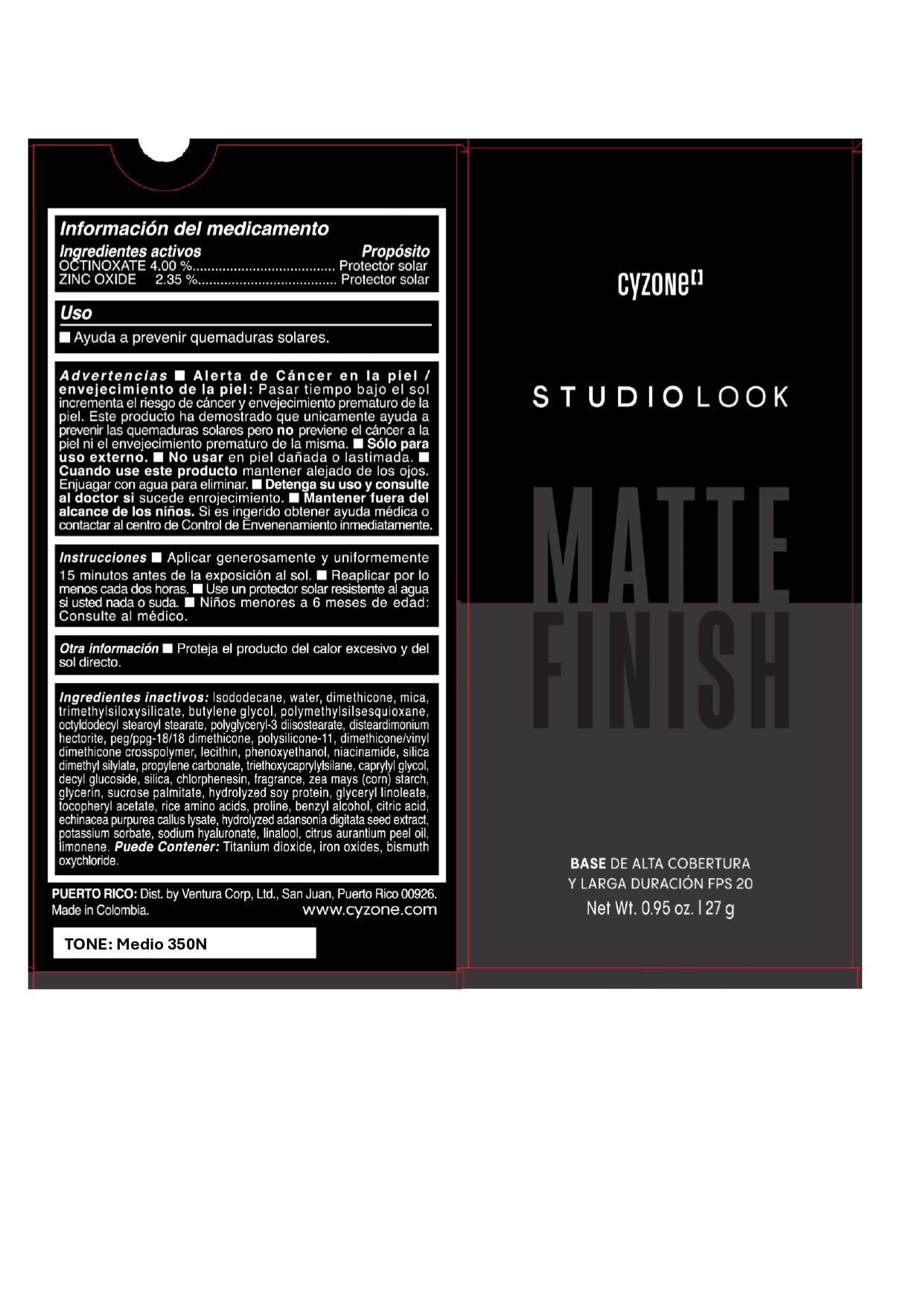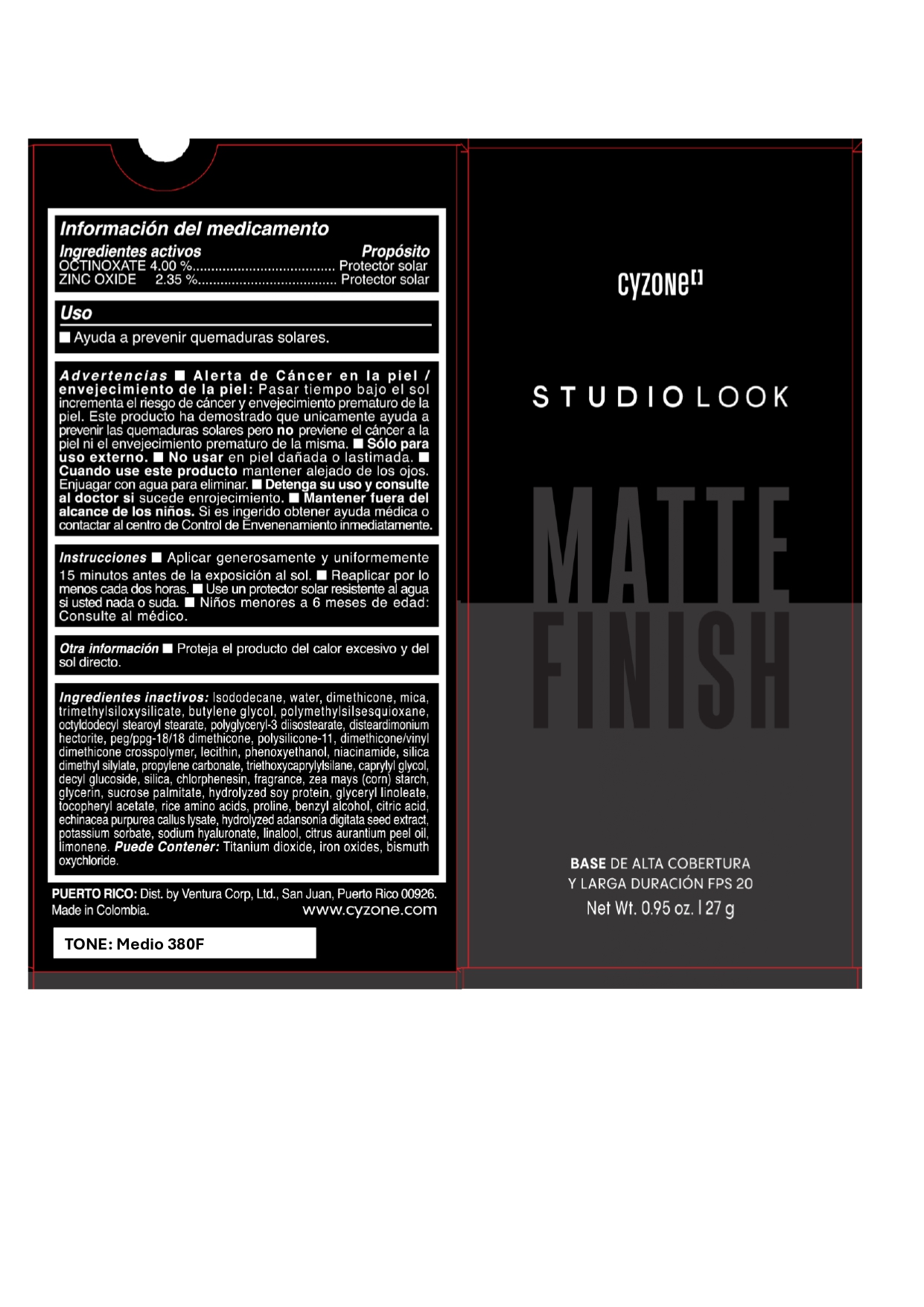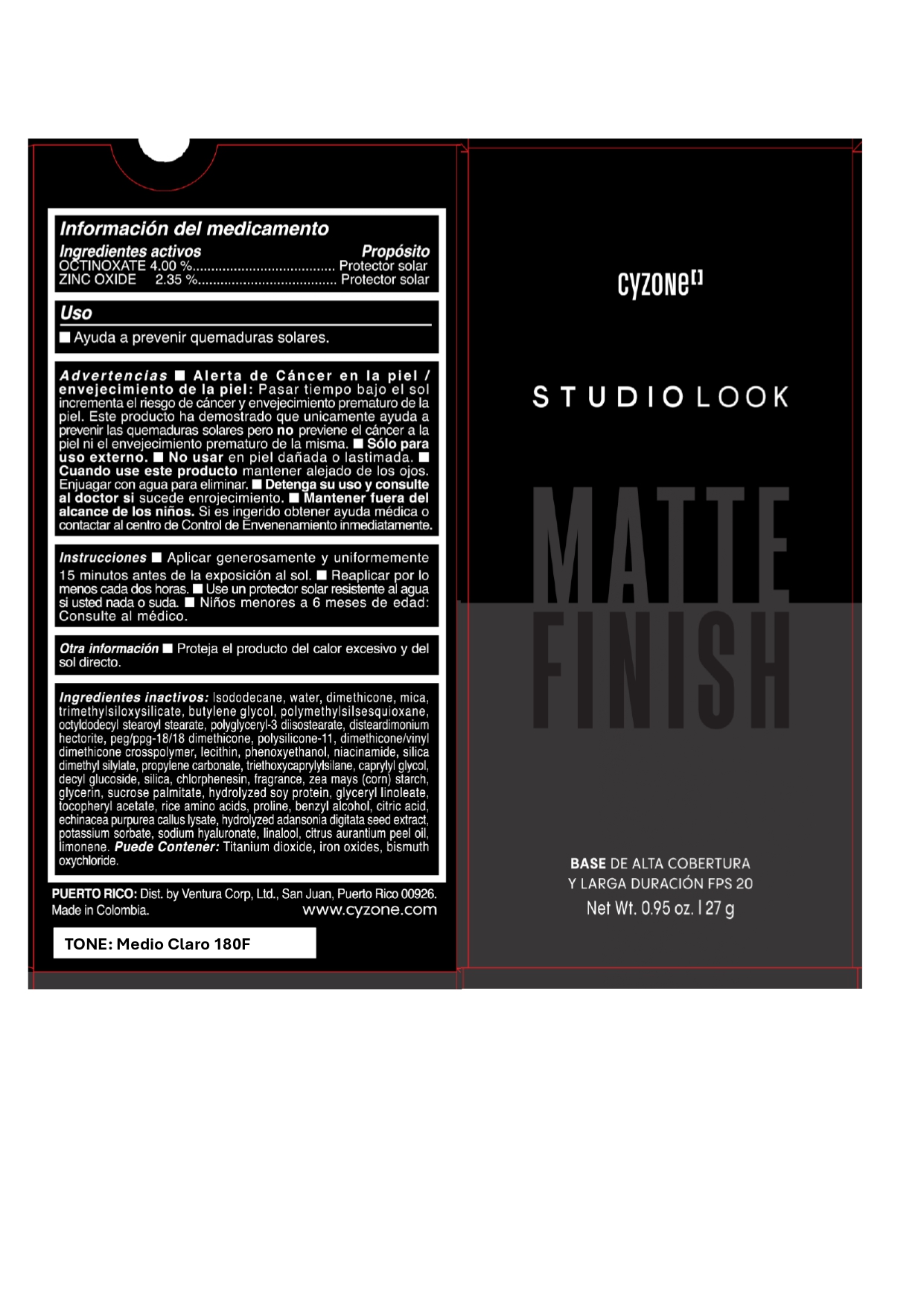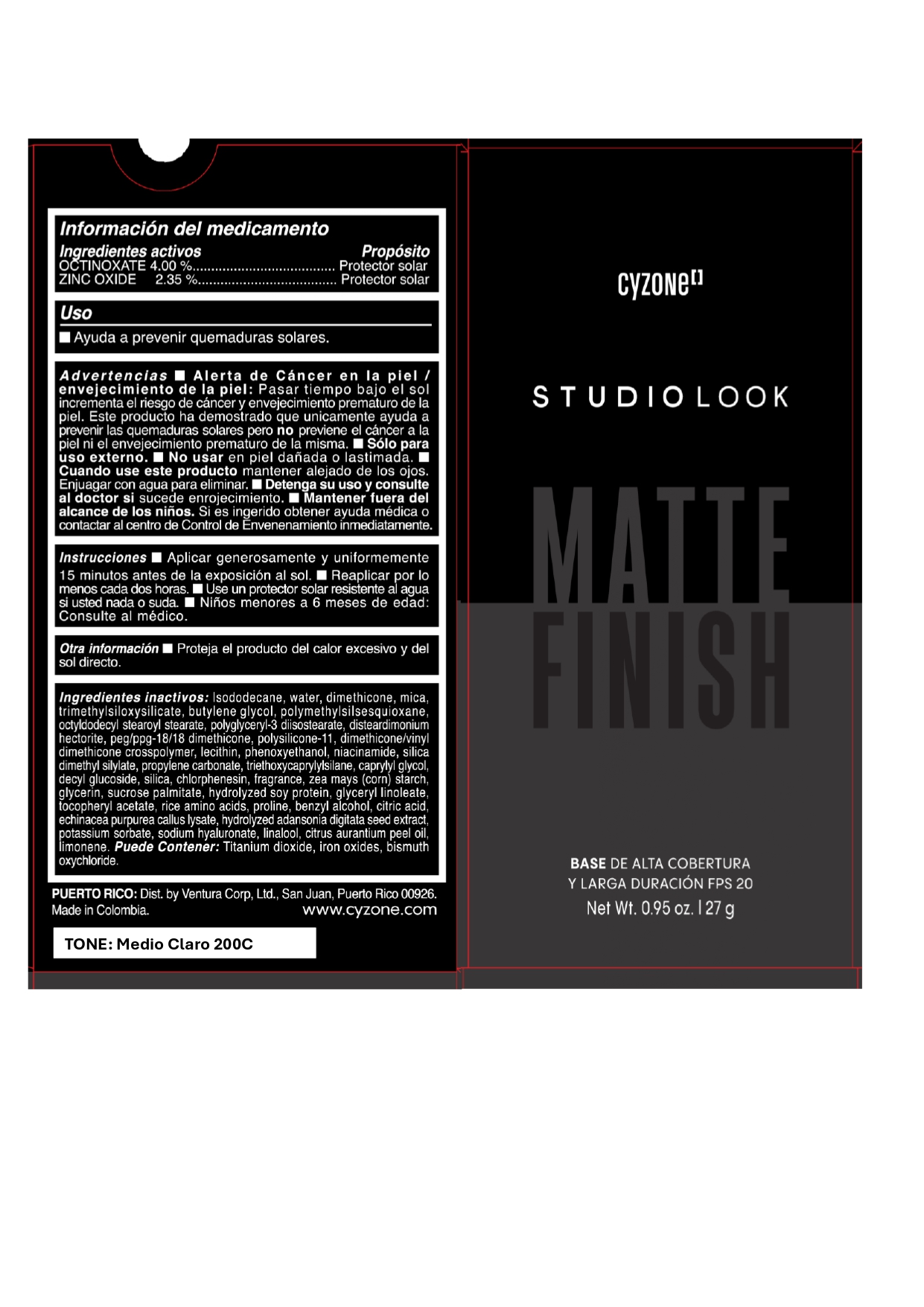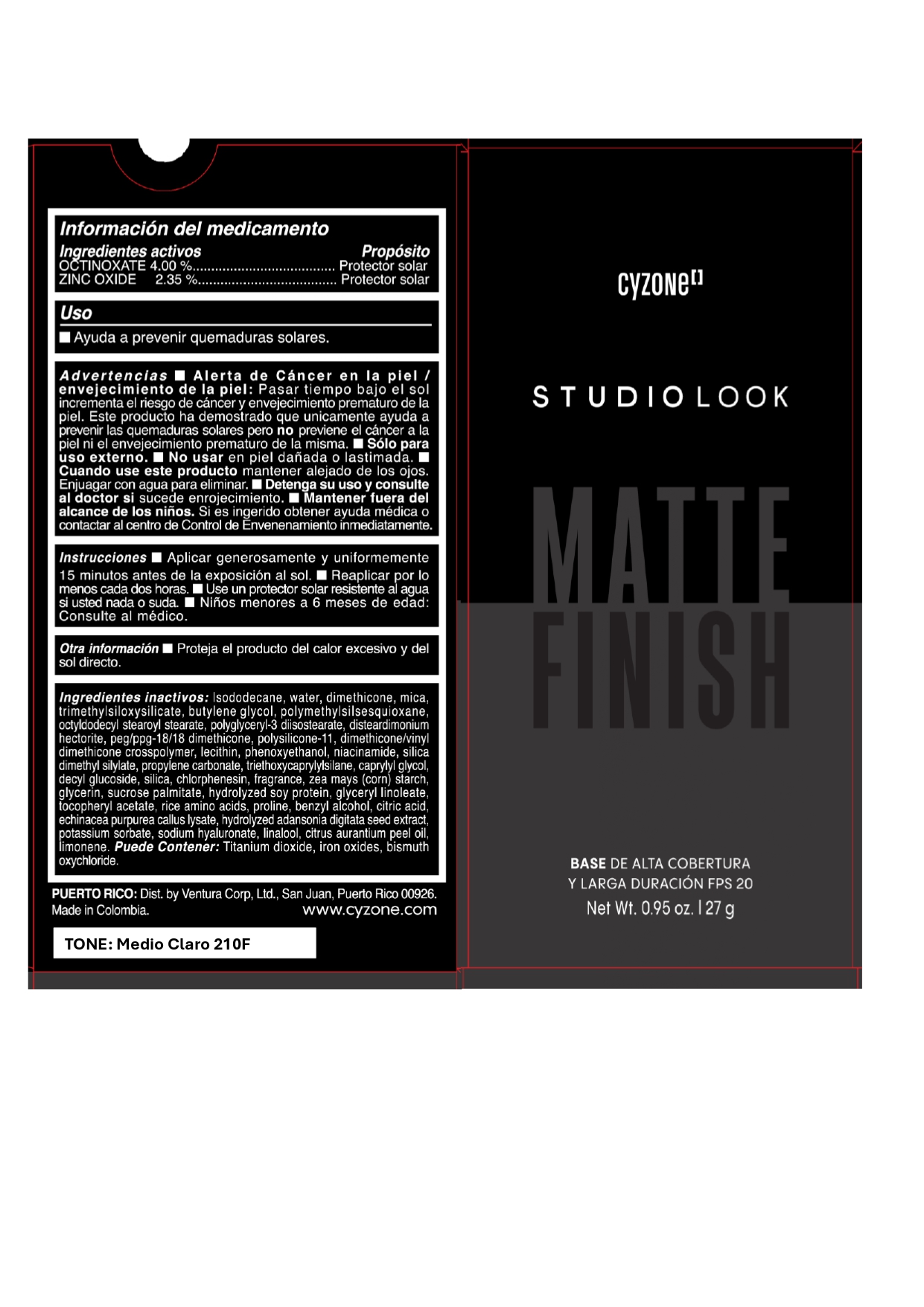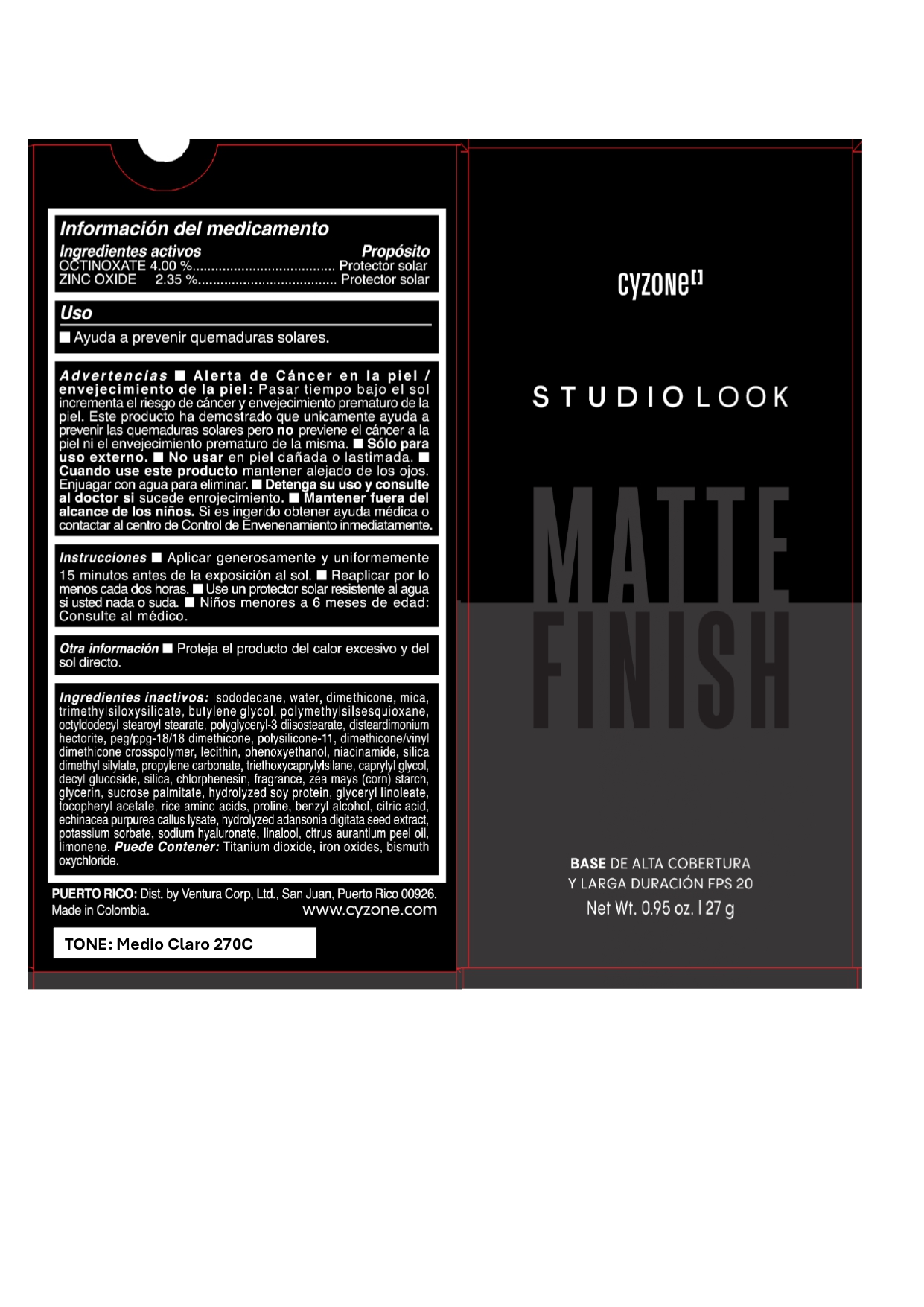 DRUG LABEL: CYZONE STUDIO LOOK MATTE FINISH BASE DE ALTA COBERTURA Y LARGA DURACION FPS 20 CLARO 140C
NDC: 14141-355 | Form: EMULSION
Manufacturer: BEL STAR S A
Category: otc | Type: HUMAN OTC DRUG LABEL
Date: 20241125

ACTIVE INGREDIENTS: OCTINOXATE 40 mg/1 g; ZINC OXIDE 23.5 mg/1 g
INACTIVE INGREDIENTS: SILICON DIOXIDE; ALPHA-TOCOPHEROL ACETATE; POTASSIUM SORBATE; IRON OXIDES; BISMUTH OXYCHLORIDE; PHENOXYETHANOL; ISODODECANE; WATER; DIMETHICONE; PEG/PPG-18/18 DIMETHICONE; LINALOOL; OCTYLDODECYL STEAROYL STEARATE; DIMETHICONE/VINYL DIMETHICONE CROSSPOLYMER (SOFT PARTICLE); NIACINAMIDE; SILICA DIMETHYL SILYLATE; LECITHIN, SUNFLOWER; ZEA MAYS (CORN) STARCH; CITRUS AURANTIUM PEEL OIL; DECYL GLUCOSIDE; DISTEARDIMONIUM HECTORITE; POLYMETHYLSILSESQUIOXANE; POLYGLYCERYL-3 DIISOSTEARATE; SUCROSE PALMITATE; HYDROLYZED SOY PROTEIN (ENZYMATIC; 2000 MW); GLYCERYL LINOLEATE; RICE AMINO ACIDS; PROLINE; BENZYL ALCOHOL; PROPYLENE CARBONATE; TITANIUM DIOXIDE; CAPRYLYL GLYCOL; CHLORPHENESIN; MICA; TRIMETHYLSILOXYSILICATE (M/Q 0.6-0.8); GLYCERIN; SODIUM HYALURONATE; LIMONENE, (+)-; BUTYLENE GLYCOL; CITRIC ACID MONOHYDRATE; TRIETHOXYCAPRYLYLSILANE

CYZONE STUDIO LOOK MATTE FINISH BASE DE ALTA COBERTURA Y LARGA DURACION FPS 20

Ingredientes activos

OCTINOXATAE 4.00%

ZINC OXIDE 2.35%

Propósito

Protector solar

Uso

Ayuda a prevenir quemaduras solares

Advertencias

- Alerta de Cáncer en la piel / envejecimiento de la piel : Pasar tiempo bajo el sol incrementa el riesgo de cáncer y envejecimiento prematuro de la piel. Este producto ha demostrado que unicamente ayuda a prevenir las quemaduras solares pero no previene el cáncer a la piel ni el envejecimiento prematuro de la misma.
- Sólo para uso externo.
- No usar en piel dañada o lastimada.
- Cuando use este producto mantener alejado de los ojos. Enjuagar con agua para eliminar.
- Detenga su uso y consulte al doctor si sucede enrojecimiento.

Mantener fuera del alcance de los niños.

Si es ingerido obtener ayuda médica o contactar al centro de Control de Envenenamiento inmediatamente

Instrucciones

- Aplicar generosamente y uniformemente 15 minutos antes de la exposición al sol.
- Reaplicar por lo menos cada dos horas.
- Use un protector solar resistente al agua si usted nada o suda.
- Niños menores a 6 meses de edad: Consulte al médico

Otra información

Proteja el producto del calor excesivo y del sol directo.

Ingredientes inactivos

Isododecane, water, dimethicone, mica, trimethylsiloxysilicate, butylene glycol, polymethylsilsesquioxane, octyldodecyl stearoyl stearate, polyglyceryl-3 diisostearate, disteardimonium hectorite, peg/ppg-18/18 dimethicone, polysilicone-11, dimethicone/vinyl dimethicone crosspolymer, lecithin, phenoxyethanol, niacinamide, silica dimethyl silylate, propylene carbonate, triethoxycaprylylsilane, caprylyl glycol, decyl glucoside, silica, chlorphenesin, fragrance, zea mays (corn) starch, glycerin, sucrose palmitate, hydrolyzed soy protein, glyceryl linoleate, tocopheryl acetate, rice amino acids, proline, benzyl alcohol, citric acid, echinacea purpurea callus lysate, hydrolyzed adansonia digitata seed extract, potassium sorbate, sodium hyaluronate, linalool, citrus aurantium peel oil, limonene.
Puede contener: Titanium dioxide, iron oxides, bismuth oxychloride.